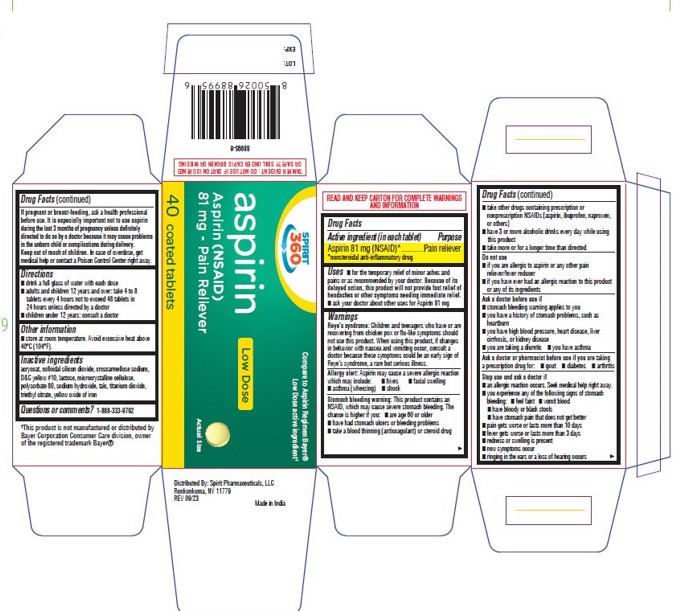 DRUG LABEL: Low Dose Aspirin
NDC: 68210-5029 | Form: TABLET, DELAYED RELEASE
Manufacturer: Spirit Pharmaceuticals LLC
Category: otc | Type: HUMAN OTC DRUG LABEL
Date: 20241213

ACTIVE INGREDIENTS: ASPIRIN 81 mg/1 1
INACTIVE INGREDIENTS: METHACRYLIC ACID; SILICON DIOXIDE; CROSCARMELLOSE SODIUM; D&C YELLOW NO. 10; LACTOSE, UNSPECIFIED FORM; MICROCRYSTALLINE CELLULOSE; POLYSORBATE 80; SODIUM HYDROXIDE; TALC; TITANIUM DIOXIDE; TRIETHYL CITRATE; FERRIC OXIDE YELLOW

ASPIRIN 81MG ADULT LOW DOSE

Directions

drink a full glass of water with each dose

adults and children 12 years and over: take 4 to 8 tablets every 4 hours not to exceed 48 tablets in 24 hours unless directed by a doctor

Other information

Store at room temparature. Avoid excessive heat above 40°C (104 °F)

Inactive ingredients

acrycoat, colloidal silicon dioxide, croscarmellose sodium, D&C yellow # 10, Lactose, microcrystalline cellulose, polysorbate 80,

sodium hydroxide, talc, titanium dioxide, triethyl citrate, yellow oxide of iron

Questions or Comments

1-888-333-9792